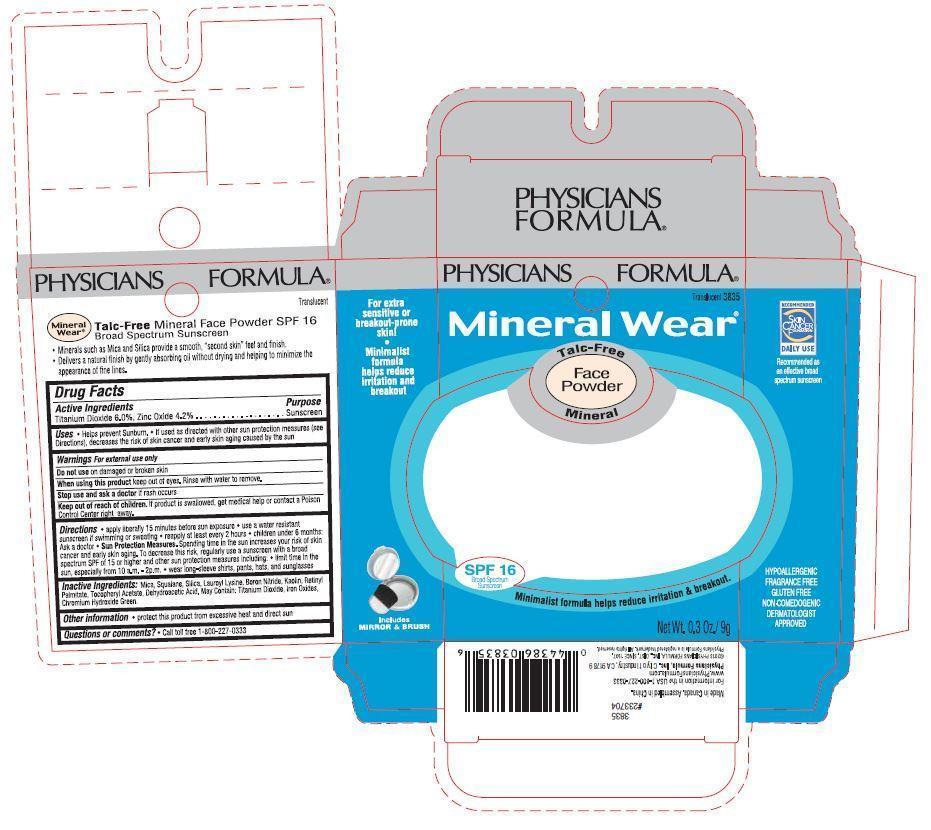 DRUG LABEL: Mineral Wear
NDC: 69184-002 | Form: POWDER
Manufacturer: Mei Shual Cosmetics Co., Ltd.
Category: otc | Type: HUMAN OTC DRUG LABEL
Date: 20141209

ACTIVE INGREDIENTS: TITANIUM DIOXIDE 6 g/100 g; ZINC OXIDE 4.2 g/100 g
INACTIVE INGREDIENTS: MICA; SQUALANE; SILICON DIOXIDE; LAUROYL LYSINE; BORON NITRIDE; KAOLIN; VITAMIN A PALMITATE; .ALPHA.-TOCOPHEROL ACETATE; DEHYDROACETIC ACID; BROWN IRON OXIDE; CHROMIUM HYDROXIDE GREEN

Active Ingredients Purpose

Titanium Dioxide 6.0%, Zinc Oxide 4.2% ....................... Sunscreen

Uses

- Helps prevent Sunburn.
- If used as directed with other sun protection measures (see Directions), decreases the risk of skin cancer and early skin aging caused by the sun.

Keep out of reach of children. If product is swallowed, get medical help or contact a Poison Control Center right away.

INDICATIONS AND USAGE

Physicians Formula

Mineral Wear

Talc-Free Mineral Face Powder

SPF 16 Broad Spectrum Sunscreen

Minimalist formula helps reduce irritation & breakout.

Net Wt. 0.3 oz / 9g

For extra sensitive or breakout-prone skin!

Recommended as an effective broad spectrum sunscreen

HYPOALLERGENIC

FRAGRANCE FREE

GLUTEN FREE

NON-COMEDOGENIC

DERMATOLOGIST APPROVED

Warnings For external use only

Do not use on damaged or broken skin

When using this product keep out of eyes. Rinse with water to remove.

Stop use and ask a doctor if rash occurs.

Directions

- apply liberally 15 minutes before sun exposure
- use a water resistant sunscreen if swimming or sweating
- reapply at least every 2 hours
- children under 6 months: Ask a doctor

Sun protection measures: spending time in the sun increases your risk of skin cancer and early skin aging. To decrease this risk, regularly use a sunscreen with a broad spectrum SPF of 15 or higher and other sun protection measures including:

- limit time in the sun, especially from 10 am - 2pm
- wear long-sleeve pants, hats, and sunglasses

Inactive Ingredients:

mica, squalane, silica, lauroyl lysine, boron nitride, kaolin, retinyl palmitate, tocopheryl acetate, dehydroacetic acid. may contain: titanium dioxide, iron oxides, chromium hydroxide green.

Other Information: protect this product from excessive heat and direct sun

Questions or comments? Call toll-free 1-800-227-0333